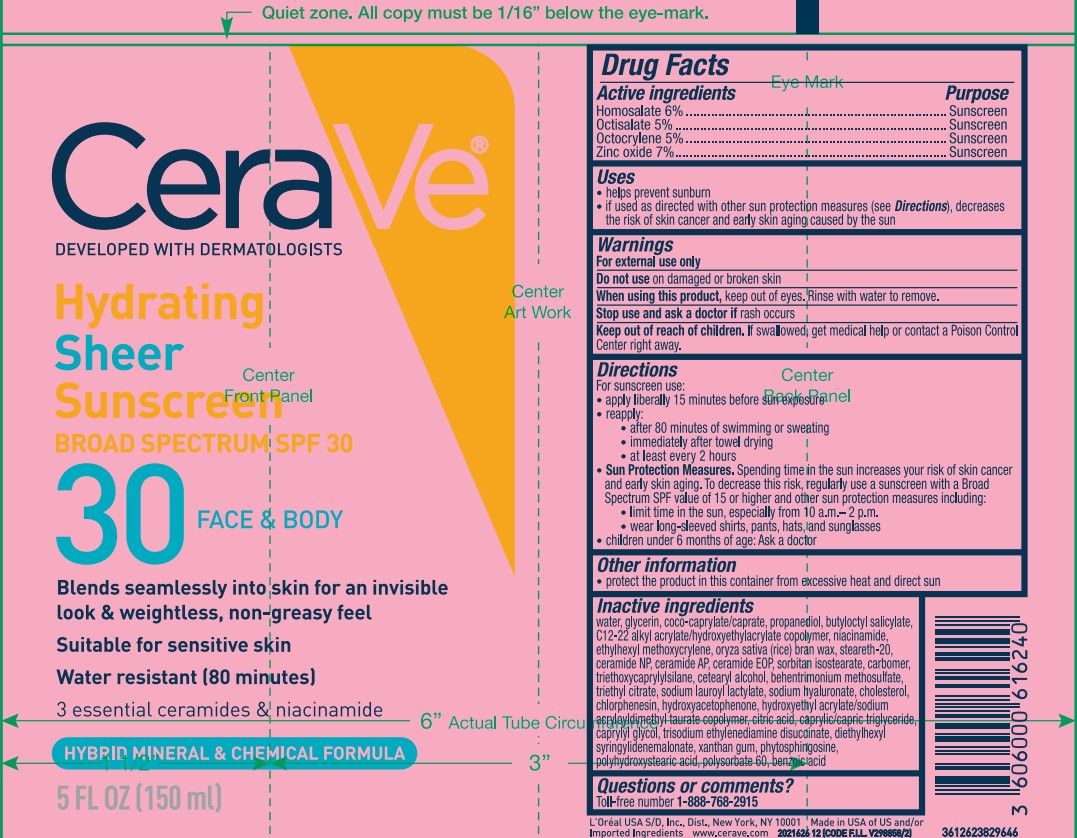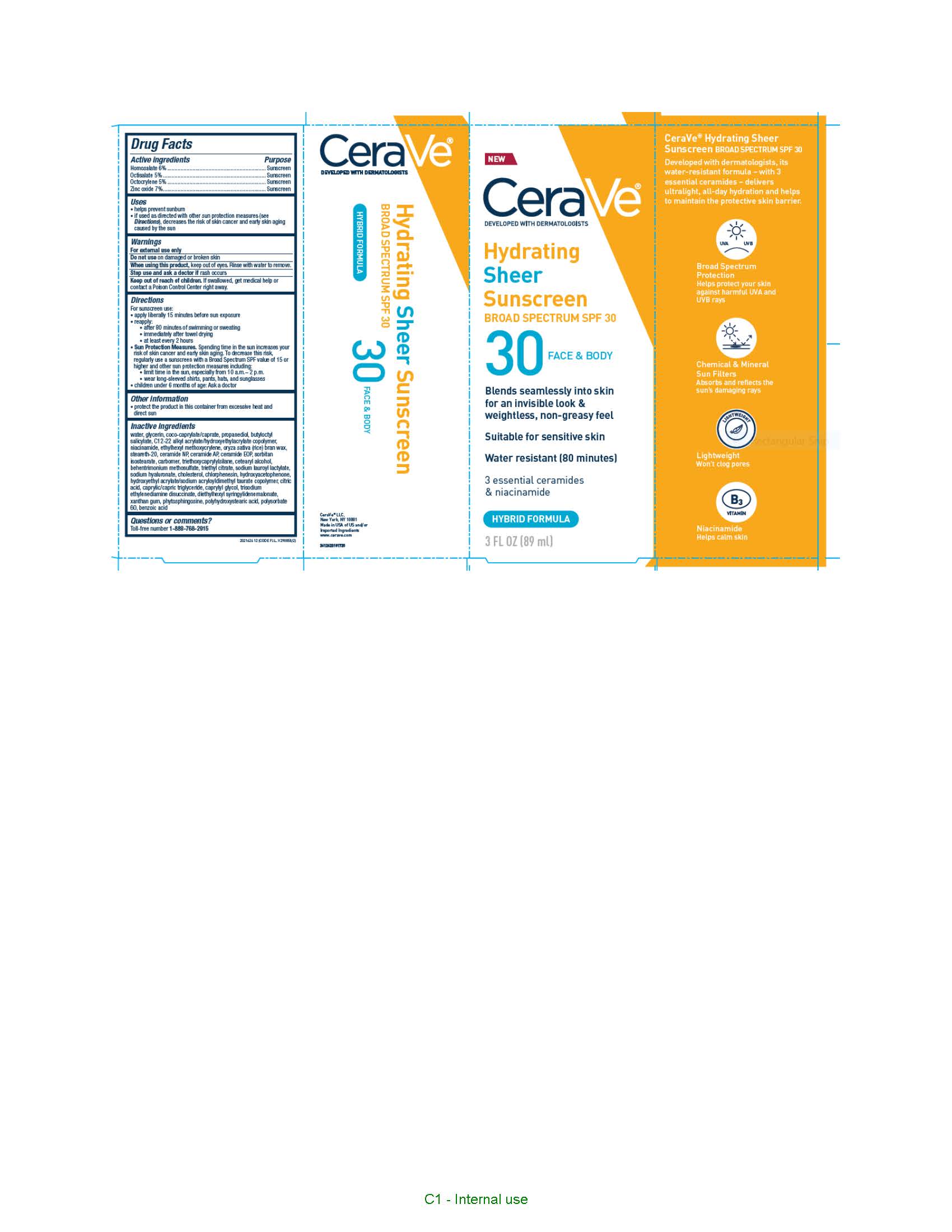 DRUG LABEL: CeraVe Developed with Dermatologists Hydrating Sheer Sunscreen Broad Spectrum SPF 30 Face and Body Water Resistant 80 Minutes Hybrid Formula
NDC: 49967-832 | Form: LOTION
Manufacturer: L'Oreal USA Products, Inc.
Category: otc | Type: HUMAN OTC DRUG LABEL
Date: 20250708

ACTIVE INGREDIENTS: HOMOSALATE 60 mg/1 mL; OCTISALATE 50 mg/1 mL; OCTOCRYLENE 50 mg/1 mL; ZINC OXIDE 70 mg/1 mL
INACTIVE INGREDIENTS: WATER; ALKYL (C12-15) BENZOATE; ISOHEXADECANE; ISONONYL ISONONANOATE; DICAPRYLYL ETHER; PEG-30 DIPOLYHYDROXYSTEARATE; TRIETHYLHEXANOIN; POLYGLYCERYL-4 ISOSTEARATE; DICAPRYLYL CARBONATE; ACRYLIC ACID/ETHYLENE COPOLYMER (600 MPA.S); TROLAMINE; SILICON DIOXIDE; STEARIC ACID; CERAMIDE NP; CERAMIDE AP; CERAMIDE 1; CARBOMER HOMOPOLYMER TYPE B (ALLYL SUCROSE CROSSLINKED); NIACINAMIDE; CETOSTEARYL ALCOHOL; TRIETHOXYCAPRYLYLSILANE; BEHENTRIMONIUM METHOSULFATE; SODIUM CHLORIDE; SALICYLIC ACID; HYALURONATE SODIUM; SODIUM LAUROYL LACTYLATE; CHOLESTEROL; ALUMINUM STEARATE; ALUMINUM OXIDE; ALUMINUM HYDROXIDE; FERRIC OXIDE RED; PHENOXYETHANOL; P-ANISIC ACID; CHLORPHENESIN; TOCOPHEROL; EDETATE DISODIUM; DISODIUM STEAROYL GLUTAMATE; PROPYLENE CARBONATE; CITRIC ACID MONOHYDRATE; CAPRYLYL GLYCOL; CAPRYLOYL SALICYLIC ACID; MEDIUM-CHAIN TRIGLYCERIDES; DIETHYLHEXYL SYRINGYLIDENEMALONATE; DISTEARDIMONIUM HECTORITE; XANTHAN GUM; PHYTOSPHINGOSINE; PHYTOSPHINGOSINE HYDROCHLORIDE; ETHYLHEXYLGLYCERIN

Drug Facts

Active ingredients

Homosalate 6%

Octisalate 5%

Octocrylene 5%

Zinc oxide 7%

Purpose

Sunscreen

Uses

• helps prevent sunburn
• if used as directed with other sun protection measures (see Directions), decreases the risk of skin cancer and early skin aging caused by the sun

Warnings

For external use only

Do not use

on damaged or broken skin

When using this product

keep out of eyes. Rinse with water to remove.

Stop use and ask a doctor if

rash occurs

Keep out of reach of children.

If swallowed, get medical help or contact a Poison Control Center right away.

Directions

For sunscreen use:
● apply liberally 15 minutes before sun exposure
● reapply:

- after 80 minutes or swimming or sweating
- immediately after towl drying
- at least every 2 hours

● Sun Protection Measures. Spending time in the sun increases your risk of skin cancer and early skin aging. To decrease this risk, regularly use a sunscreen with a Broad Spectrum SPF value of 15 or higher and other sun protection measures including:
● limit time in the sun, especially from 10 a.m. – 2 p.m.
● wear long-sleeved shirts, pants, hats, and sunglasses
● children under 6 months of age: Ask a doctor

Inactive ingredients

water, c12-15 alkyl benzoate, isohexadecane, isononyl isononanoate, dicaprylyl ether, PEG-30 dipolyhydroxystearate, triethylhexanoin, polyglyceryl-4 isostearate, dicaprylyl carbonate, ethylene/acrylic acid copolymer, triethanolamine, silica, poly c10-30 alkyl acrylate, stearic acid, ceramide NP, ceramide AP, ceramide EOP, carbomer, niacinamide, cetearyl alcohol, triethoxycaprylylsilane, behentrimonium methosulfate, sodium chloride, salicylic acid, sodium hyaluronate, sodium lauroyl lactylate, cholesterol, aluminum stearate, alumina, aluminum hydroxide, iron oxides, phenoxyethanol, p-anisic acid, chlorphenesin, tocoferol, disodium EDTA, disodium stearoyl glutamate, propylene carbonate, citric acid, caprylyl glycol, capryloyl salicylic acid, caprylic/capric triglyceride, diethylhexyl syringylidenemalonate, disteardimonium hectorite, xanthan gum, phytosphingosine, polyhydroxystearic acid, ethylhexylglycerin

Other information

protect the product in this container from excessive heat and direct sun

Questions or comments?

Toll-free number 1-888-768-2915

www.CeraVe.com